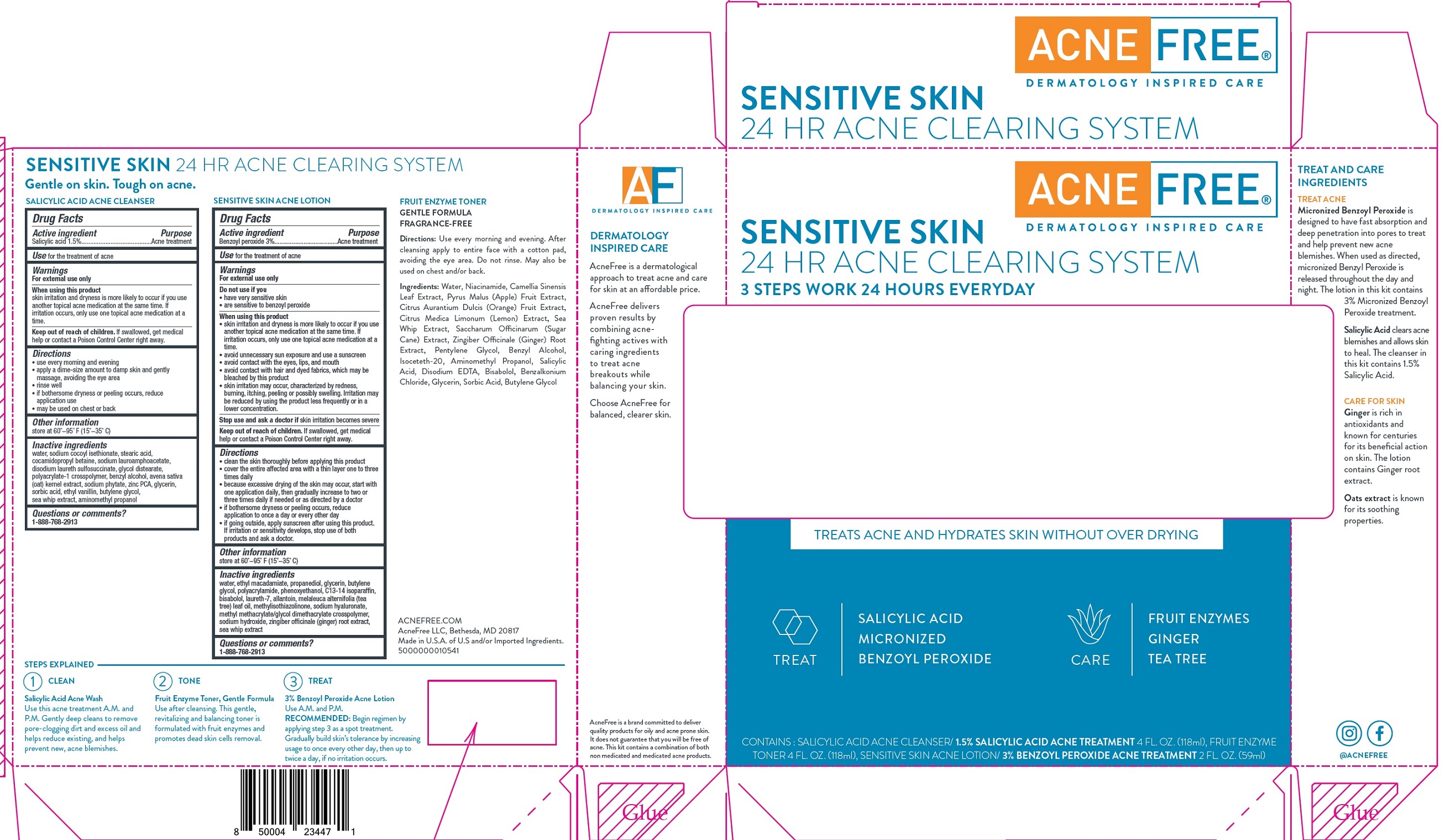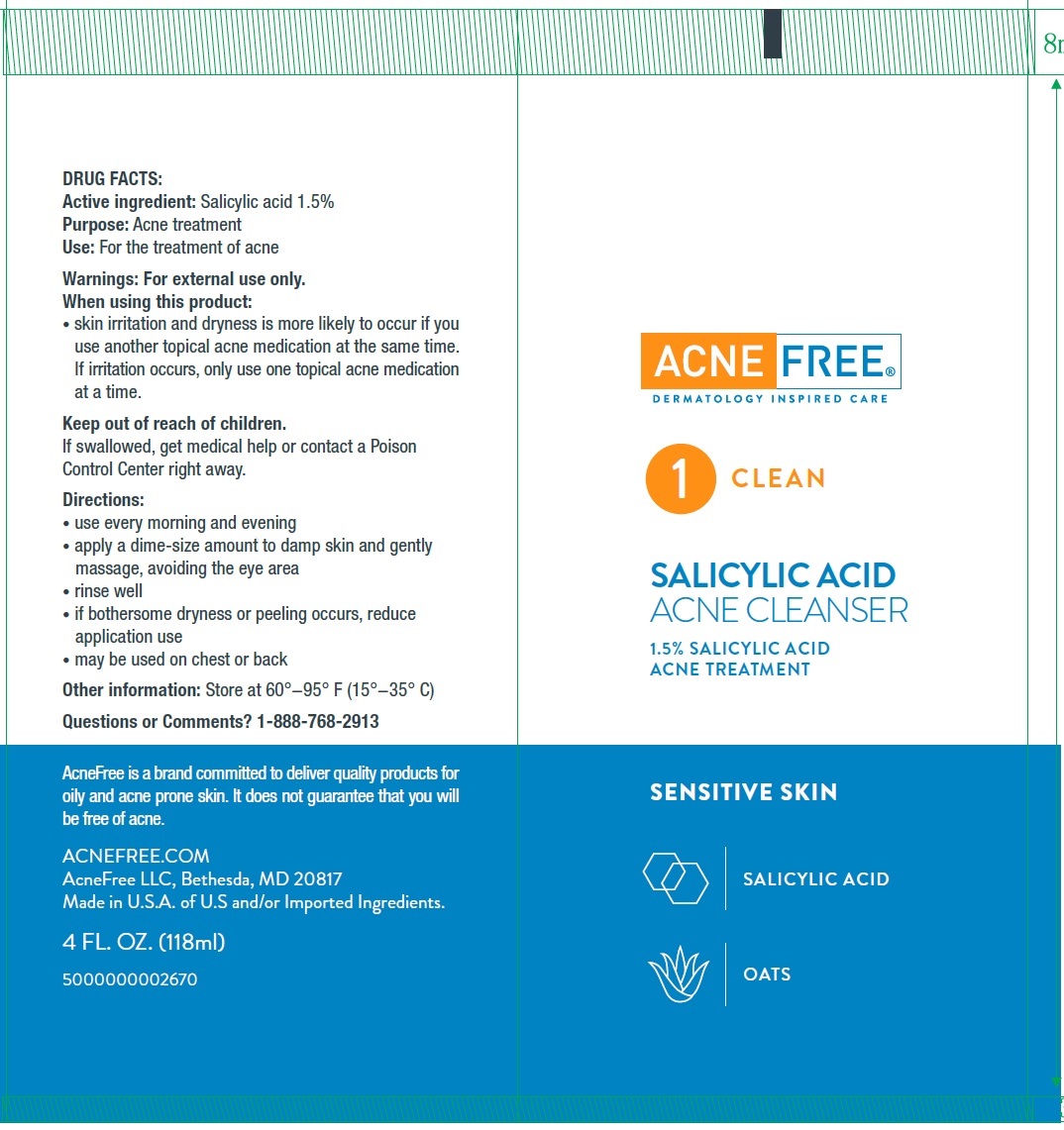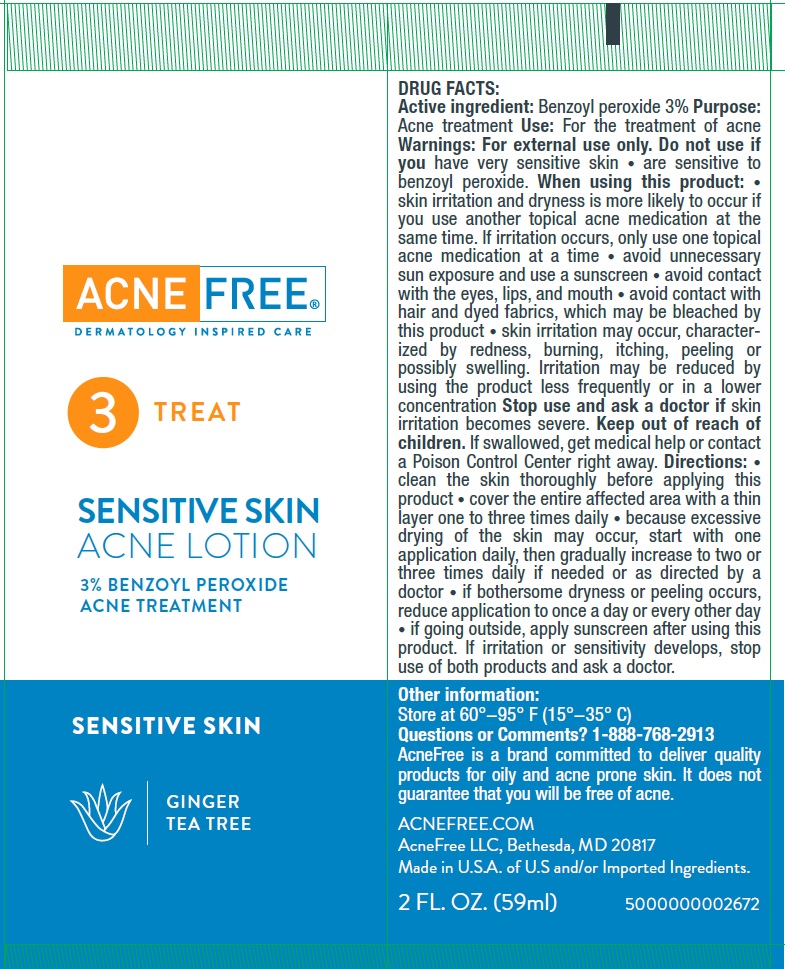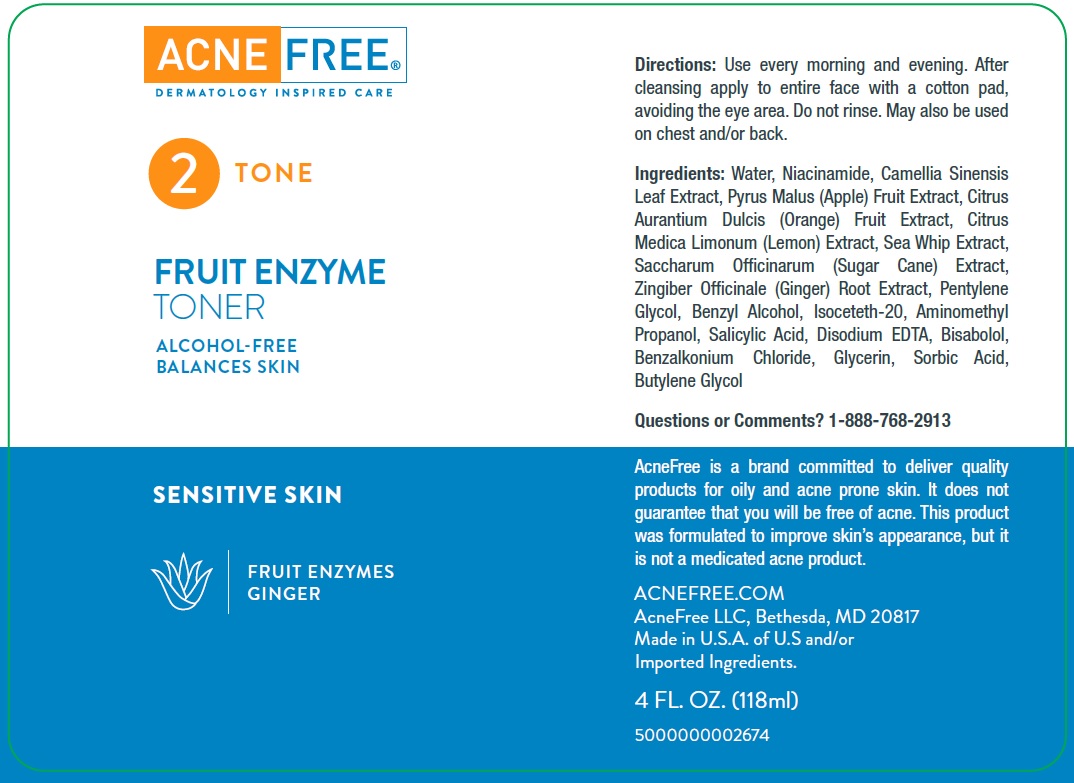 DRUG LABEL: Acne Free SENSITIVE SKIN 24 HR Acne Clearing System
NDC: 80861-007 | Form: KIT | Route: TOPICAL
Manufacturer: AcneFree LLC
Category: otc | Type: HUMAN OTC DRUG LABEL
Date: 20250724

ACTIVE INGREDIENTS: SALICYLIC ACID 15 mg/1 mL; BENZOYL PEROXIDE 30 mg/1 mL
INACTIVE INGREDIENTS: WATER; SODIUM COCOYL ISETHIONATE; STEARIC ACID; COCAMIDOPROPYL BETAINE; SODIUM LAUROAMPHOACETATE; DISODIUM LAURETH SULFOSUCCINATE; GLYCOL DISTEARATE; BENZYL ALCOHOL; OAT; PHYTATE SODIUM; ZINC PIDOLATE; GLYCERIN; SORBIC ACID; ETHYL VANILLIN; BUTYLENE GLYCOL; PSEUDOPTEROGORGIA ELISABETHAE; AMINOMETHYLPROPANOL; WATER; ETHYL MACADAMIATE; PROPANEDIOL; GLYCERIN; BUTYLENE GLYCOL; PHENOXYETHANOL; C13-14 ISOPARAFFIN; LEVOMENOL; LAURETH-7; ALLANTOIN; TEA TREE OIL; METHYLISOTHIAZOLINONE; HYALURONATE SODIUM; METHYL METHACRYLATE/GLYCOL DIMETHACRYLATE CROSSPOLYMER; SODIUM HYDROXIDE; GINGER; PSEUDOPTEROGORGIA ELISABETHAE

Acne Free SENSITIVE SKIN 24 HR Acne Clearing System KIT

Active ingredient

Salicylic acid 1.5%

Purpose

Acne treatment

Use

for the treatment of acne

Warnings

For external use only

When using this product

skin irritation and dryness is more likely to occur if you use another topical acne medication at the same time. If irritation occurs, only use one topical acne medication at a time.

Keep out of reach of children.

If swallowed, get medical help or contact a Poison Control Center right away.

Directions

• use every morning and evening
• apply a dime-size amount to damp skin and gently massage, avoiding the eye area
• rinse well
• if bothersome dryness or peeling occurs, reduce application use
• may be used on chest or back

Other information

store at 60°−95° F (15°−35° C)

Inactive ingredients

water, sodium cocoyl isethionate, stearic acid, cocamidopropyl betaine, sodium lauroamphoacetate, disodium laureth sulfosuccinate, glycol distearate, polyacrylate-1 crosspolymer, benzyl alcohol, avena sativa (oat) kernel extract, sodium phytate, zinc PCA, glycerin, sorbic acid, ethyl vanillin, butylene glycol, sea whip extract, aminomethyl propanol

Questions or comments?

1-888-768-2913

Active ingredient

Benzoyl peroxide 3%

Purpose

Acne treatment

Use

for the treatment of acne

Warnings

For external use only

Do not use

if you

• have very sensitive skin
• are sensitive to benzoyl peroxide

When using this product

• skin irritation and dryness is more likely to occur if you use another topical acne medication at the same time. If irritation occurs, only use one topical acne medication at a time.
• avoid unnecessary sun exposure and use a sunscreen
• avoid contact with the eyes, lips, and mouth
• avoid contact with hair and dyed fabrics, which may be bleached by this product
• skin irritation may occur, characterized by redness, burning, itching, peeling or possibly swelling. Irritation may be reduced by using the product less frequently or in a lower concentration.

Stop use and ask a doctor if

skin irritation becomes severe

Keep out of reach of children.

If swallowed, get medical help or contact a Poison Control Center right away.

Directions

• clean the skin thoroughly before applying this product
• cover the entire affected area with a thin layer one to three times daily • because excessive drying of the skin may occur, start with one application daily, then gradually increase to two or three times daily if needed or as directed by a doctor
• if bothersome dryness or peeling occurs, reduce application to once a day or every other day
• if going outside, apply sunscreen after using this product. If irritation or sensitivity develops, stop use of both products and ask a doctor.

Other information

store at 60°−95° F (15°−35° C)

Inactive ingredients

water, ethyl macadamiate, propanediol, glycerin, butylene glycol, polyacrylamide, phenoxyethanol, C13-14 isoparaffin, bisabolol, laureth-7, allantoin, melaleuca alternifolia (tea tree) leaf oil, methylisothiazolinone, sodium hyaluronate, methyl methacrylate/glycol dimethacrylate crosspolymer, sodium hydroxide

Questions or comments?

1-888-768-2913